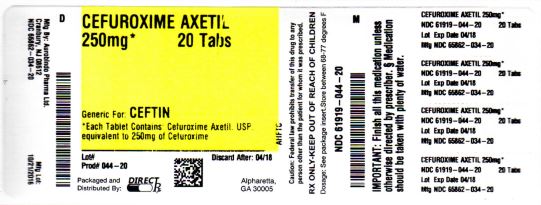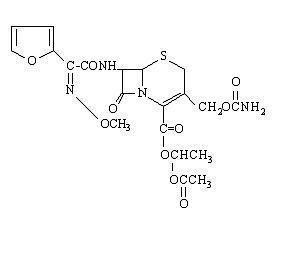 DRUG LABEL: CEFUROXIME AXETIL
NDC: 61919-044 | Form: TABLET
Manufacturer: DIRECT RX
Category: prescription | Type: HUMAN PRESCRIPTION DRUG LABEL
Date: 20200117

ACTIVE INGREDIENTS: CEFUROXIME AXETIL 250 mg/1 1
INACTIVE INGREDIENTS: SILICON DIOXIDE; CROSCARMELLOSE SODIUM; HYDROGENATED COTTONSEED OIL; CELLULOSE, MICROCRYSTALLINE; SODIUM LAURYL SULFATE

CEFUROXIME AXETIL

DESCRIPTION SECTION

Cefuroxime axetil tablets contain cefuroxime as cefuroxime axetil. Cefuroxime axetil is a semisynthetic, broad-spectrum cephalosporin antibiotic for oral administration.

Chemically, cefuroxime axetil, the 1-(acetyloxy) ethyl ester of cefuroxime, is (RS)-1-hydroxyethyl (6R,7R)-7-[2-(2-furyl)glyoxyl-amido]-3-(hydroxymethyl)-8-oxo-5-thia-1-azabicyclo[4.2.0]-oct-2-ene-2-carboxylate, 72-(Z)-(O-methyl-oxime), 1-acetate 3-carbamate. Its molecular formula is C20H22N4O10S, and it has a molecular weight of 510.48.

Cefuroxime axetil is in the amorphous form and has the following structural formula:

Cefuroxime axetil tablets are uncoated and contain the equivalent of 125, 250 or 500 mg of cefuroxime as cefuroxime axetil. Cefuroxime axetil tablets contain the inactive ingredients colloidal silicon dioxide, croscarmellose sodium, hydrogenated vegetable oil, microcrystalline cellulose, and sodium lauryl sulfate.

CLINICAL PHARMACOLOGY SECTION

Absorption and Metabolism

After oral administration, cefuroxime axetil is absorbed from the gastrointestinal tract and rapidly hydrolyzed by nonspecific esterases in the intestinal mucosa and blood to cefuroxime. Cefuroxime is subsequently distributed throughout the extracellular fluids. The axetil moiety is metabolized to acetaldehyde and acetic acid.

Pharmacokinetics

Approximately 50% of serum cefuroxime is bound to protein. Serum pharmacokinetic parameters for cefuroxime axetil tablets are shown in Table 1.

Table 1. Postprandial Pharmacokinetics of Cefuroxime Administered as Cefuroxime Axetil Tablets to Adults*
Dose† (Cefuroxime Equivalent) | Peak Plasma Concentration (mcg/mL) | Time of Peak Plasma Concentration (hr) | Mean Elimination Half-Life (hr) | AUC (mcg-hr mL)
125 mg | 2.1 | 2.2 | 1.2 | 6.7
250 mg | 4.1 | 2.5 | 1.2 | 12.9
500 mg | 7 | 3 | 1.2 | 27.4
1,000 mg | 13.6 | 2.5 | 1.3 | 50
*Mean values of 12 healthy adult volunteers.
† Drug administered immediately after a meal.

Comparative Pharmacokinetic Properties: Cefuroxime axetil for oral suspension was not bioequivalent to cefuroxime axetil tablets when tested in healthy adults. The tablet and powder for oral suspension formulations are NOT substitutable on a milligram-per-milligram basis. The area under the curve for the suspension averaged 91% of that for the tablet, and the peak plasma concentration for the suspension averaged 71% of the peak plasma concentration of the tablets. Therefore, the safety and effectiveness of both the tablet and oral suspension formulations had to be established in separate clinical trials.

Food Effect on Pharmacokinetics

Absorption of the tablet is greater when taken after food (absolute bioavailability of cefuroxime axetil tablets increases from 37% to 52%). Despite this difference in absorption, the clinical and bacteriologic responses of patients were independent of food intake at the time of tablet administration in 2 studies where this was assessed.

Renal Excretion

Cefuroxime is excreted unchanged in the urine; in adults, approximately 50% of the administered dose is recovered in the urine within 12 hours. The pharmacokinetics of cefuroxime in the urine of pediatric patients have not been studied at this time. Until further data are available, the renal pharmacokinetic properties of cefuroxime axetil established in adults should not be extrapolated to pediatric patients.

Because cefuroxime is renally excreted, the serum half-life is prolonged in patients with reduced renal function. In a study of 20 elderly patients (mean age = 83.9 years) having a mean creatinine clearance of 34.9 mL/min, the mean serum elimination half-life was 3.5 hours. Despite the lower elimination of cefuroxime in geriatric patients, dosage adjustment based on age is not necessary (see PRECAUTIONS: Geriatric Use).

Microbiology

The in vivo bactericidal activity of cefuroxime axetil is due to cefuroxime’s binding to essential target proteins and the resultant inhibition of cell-wall synthesis.

Cefuroxime has bactericidal activity against a wide range of common pathogens, including many beta-lactamase–producing strains. Cefuroxime is stable to many bacterial beta-lactamases, especially plasmid-mediated enzymes that are commonly found in enterobacteriaceae.

Cefuroxime has been demonstrated to be active against most strains of the following microorganisms both in vitro and in clinical infections as described in the INDICATIONS AND USAGE section (see INDICATIONS AND USAGE section).

Aerobic Gram-Positive Microorganisms

Staphylococcus aureus (including beta-lactamase–producing strains)

Streptococcus pneumoniae

Streptococcus pyogenes

Aerobic Gram-Negative Microorganisms

Escherichia coli

Haemophilus influenzae (including beta-lactamase–producing strains)

Haemophilus parainfluenzae

Klebsiella pneumoniae

Moraxella catarrhalis (including beta-lactamase–producing strains)

Neisseria gonorrhoeae (including beta-lactamase–producing strains)

Spirochetes

Borrelia burgdorferi

Cefuroxime has been shown to be active in vitro against most strains of the following microorganisms; however, the clinical significance of these findings is unknown.

Cefuroxime exhibits in vitro minimum inhibitory concentrations (MICs) of 4 mcg/mL or less (systemic susceptible breakpoint) against most (≥90%) strains of the following microorganisms; however, the safety and effectiveness of cefuroxime in treating clinical infections due to these microorganisms have not been established in adequate and well-controlled trials.

Aerobic Gram-Positive Microorganisms

Staphylococcus epidermidis

Staphylococcus saprophyticus

Streptococcus agalactiae

NOTE: Listeria monocytogenes and certain strains of enterococci, e.g., Enterococcus faecalis (formerly Streptococcus faecalis), are resistant to cefuroxime. Methicillin-resistant staphylococci are resistant to cefuroxime.

Aerobic Gram-Negative Microorganisms

Morganella morganii

Proteus inconstans

Proteus mirabilis

Providencia rettgeri

NOTE: Pseudomonas spp., Campylobacter spp., Acinetobacter calcoaceticus, Legionella spp., and most strains of Serratia spp. and Proteus vulgaris are resistant to most first- and second-generation cephalosporins. Some strains of Morganella morganii, Enterobacter cloacae, and Citrobacter spp. have been shown by in vitro tests to be resistant to cefuroxime and other cephalosporins.

Anaerobic Microorganisms

Peptococcus niger

NOTE: Most strains of Clostridium difficile and Bacteroides fragilis are resistant to cefuroxime.

Susceptibility TestsDilution Techniques

Quantitative methods that are used to determine MICs provide reproducible estimates of the susceptibility of bacteria to antimicrobial compounds. One such standardized procedure uses a standardized dilution method1 (broth, agar, or microdilution) or equivalent with cefuroxime powder. The MIC values obtained should be interpreted according to the following criteria:

MIC (mcg/mL) | Interpretation
≤4 | (S) Susceptible
8-16 | (I) Intermediate
≥32 | (R) Resistant

A report of “Susceptible” indicates that the pathogen, if in the blood, is likely to be inhibited by usually achievable concentrations of the antimicrobial compound in blood. A report of “Intermediate” indicates that inhibitory concentrations of the antibiotic may be achieved if high dosage is used or if the infection is confined to tissues or fluids in which high antibiotic concentrations are attained. This category also provides a buffer zone that prevents small, uncontrolled technical factors from causing major discrepancies in interpretation. A report of “Resistant” indicates that usually achievable concentrations of the antimicrobial compound in the blood are unlikely to be inhibitory and that other therapy should be selected.

Standardized susceptibility test procedures require the use of laboratory control microorganisms. Standard cefuroxime powder should give the following MIC values:

Microorganism | MIC (mcg/mL)
Escherichia coli ATCC 25922 | 2-8
Staphylococcus aureus ATCC 29213 | 0.5-2

Diffusion Techniques

Quantitative methods that require measurement of zone diameters provide estimates of the susceptibility of bacteria to antimicrobial compounds. One such standardized procedure2 that has been recommended (for use with disks) to test the susceptibility of microorganisms to cefuroxime uses the 30 mcg cefuroxime disk. Interpretation involves correlation of the diameter obtained in the disk test with the MIC for cefuroxime.

Reports from the laboratory providing results of the standard single-disk susceptibility test with a 30 mcg cefuroxime disk should be interpreted according to the following criteria:

Zone Diameter (mm) | Interpretation
≥23 | (S) Susceptible
15-22 | (I) Intermediate
≤14 | (R) Resistant

Interpretation should be as stated above for results using dilution techniques.

As with standard dilution techniques, diffusion methods require the use of laboratory control microorganisms. The 30 mcg cefuroxime disk provides the following zone diameters in these laboratory test quality control strains:

Microorganism | Zone Diameter (mm)
Escherichia coli ATCC 25922 | 20-26
Staphylococcus aureus ATCC 25923 | 27-35

INDICATIONS & USAGE SECTION

To reduce the development of drug-resistant bacteria and maintain the effectiveness of cefuroxime axetil and other antibacterial drugs, cefuroxime axetil should be used only to treat or prevent infections that are proven or strongly suspected to be caused by susceptible bacteria. When culture and susceptibility information are available, they should be considered in selecting or modifying antibacterial therapy. In the absence of such data, local epidemiology and susceptibility patterns may contribute to the empiric selection of therapy.

NOTE: CEFUROXIME AXETIL TABLETS AND CEFUROXIME AXETIL FOR ORAL SUSPENSION ARE NOT BIOEQUIVALENT AND ARE NOT SUBSTITUTABLE ON A MILLIGRAM-PER-MILLIGRAM BASIS (SEE CLINICAL PHARMACOLOGY).

Cefuroxime Axetil Tablets

Cefuroxime axetil tablets are indicated for the treatment of patients with mild to moderate infections caused by susceptible strains of the designated microorganisms in the conditions listed below:

1. Pharyngitis/Tonsillitis caused by Streptococcus pyogenes.
  NOTE: The usual drug of choice in the treatment and prevention of streptococcal infections, including the prophylaxis of rheumatic fever, is penicillin given by the intramuscular route. Cefuroxime axetil tablets are generally effective in the eradication of streptococci from the nasopharynx; however, substantial data establishing the efficacy of cefuroxime in the subsequent prevention of rheumatic fever are not available. Please also note that in all clinical trials, all isolates had to be sensitive to both penicillin and cefuroxime. There are no data from adequate and well-controlled trials to demonstrate the effectiveness of cefuroxime in the treatment of penicillin-resistant strains of Streptococcus pyogenes.
2. Acute Bacterial Otitis Media caused by Streptococcus pneumoniae, Haemophilus influenzae (including beta-lactamase–producing strains), Moraxella catarrhalis (including beta-lactamase–producing strains), or Streptococcus pyogenes.
3. Acute Bacterial Maxillary Sinusitis caused by Streptococcus pneumoniae or Haemophilus influenzae (non-beta-lactamase–producing strains only). (See CLINICAL STUDIES section.)
  NOTE: In view of the insufficient numbers of isolates of beta-lactamase–producing strains of Haemophilus influenzae and Moraxella catarrhalis that were obtained from clinical trials with cefuroxime axetil tablets for patients with acute bacterial maxillary sinusitis, it was not possible to adequately evaluate the effectiveness of cefuroxime axetil tablets for sinus infections known, suspected, or considered potentially to be caused by beta-lactamase–producing Haemophilus influenzae or Moraxella catarrhalis.
4. Acute Bacterial Exacerbations of Chronic Bronchitis and Secondary Bacterial Infections of Acute Bronchitis caused by Streptococcus pneumoniae, Haemophilus influenzae (beta-lactamase negative strains), or Haemophilus parainfluenzae (beta-lactamase negative strains). (See DOSAGE AND ADMINISTRATION section and CLINICAL STUDIES section.)
5. Uncomplicated Skin and Skin-Structure Infections caused by Staphylococcus aureus (including beta-lactamase–producing strains) or Streptococcus pyogenes.
6. Uncomplicated Urinary Tract Infections caused by Escherichia coli or Klebsiella pneumoniae.
7. Uncomplicated Gonorrhea, urethral and endocervical, caused by penicillinase-producing and non-penicillinase–producing strains of Neisseria gonorrhoeae and uncomplicated gonorrhea, rectal, in females, caused by non-penicillinase–producing strains of Neisseria gonorrhoeae.
8. Early Lyme Disease (erythema migrans) caused by Borrelia burgdorferi.

CONTRAINDICATIONS

Cefuroxime axetil products are contraindicated in patients with known allergy to the cephalosporin group of antibiotics.

WARNINGS SECTION

CEFUROXIME AXETIL TABLETS AND CEFUROXIME AXETIL FOR ORAL SUSPENSION ARE NOT BIOEQUIVALENT AND ARE THEREFORE NOT SUBSTITUTABLE ON A MILLIGRAM-PER-MILLIGRAM BASIS (SEE CLINICAL PHARMACOLOGY).

BEFORE THERAPY WITH CEFUROXIME AXETIL PRODUCTS IS INSTITUTED, CAREFUL INQUIRY SHOULD BE MADE TO DETERMINE WHETHER THE PATIENT HAS HAD PREVIOUS HYPERSENSITIVITY REACTIONS TO CEFUROXIME AXETIL PRODUCTS, OTHER CEPHALOSPORINS, PENICILLINS, OR OTHER DRUGS. IF THIS PRODUCT IS TO BE GIVEN TO PENICILLIN-SENSITIVE PATIENTS, CAUTION SHOULD BE EXERCISED BECAUSE CROSS-HYPERSENSITIVITY AMONG BETA-LACTAM ANTIBIOTICS HAS BEEN CLEARLY DOCUMENTED AND MAY OCCUR IN UP TO 10% OF PATIENTS WITH A HISTORY OF PENICILLIN ALLERGY. IF A CLINICALLY SIGNIFICANT ALLERGIC REACTION TO CEFUROXIME AXETIL PRODUCTS OCCURS, DISCONTINUE THE DRUG AND INSTITUTE APPROPRIATE THERAPY. SERIOUS ACUTE HYPERSENSITIVITY REACTIONS MAY REQUIRE TREATMENT WITH EPINEPHRINE AND OTHER EMERGENCY MEASURES, INCLUDING OXYGEN, INTRAVENOUS FLUIDS, INTRAVENOUS ANTIHISTAMINES, CORTICOSTEROIDS, PRESSOR AMINES, AND AIRWAY MANAGEMENT, AS CLINICALLY INDICATED.

Clostridium difficile associated diarrhea (CDAD) has been reported with use of nearly all antibacterial agents, including cefuroxime, and may range in severity from mild diarrhea to fatal colitis. Treatment with antibacterial agents alters the normal flora of the colon leading to overgrowth of C. difficile.

C. difficile produces toxins A and B which contribute to the development of CDAD. Hypertoxin producing strains of C. difficile cause increased morbidity and mortality, as these infections can be refractory to antimicrobial therapy and may require colectomy. CDAD must be considered in all patients who present with diarrhea following antibiotic use. Careful medical history is necessary since CDAD has been reported to occur over two months after the administration of antibacterial agents.

If CDAD is suspected or confirmed, ongoing antibiotic use not directed against C. difficile may need to be discontinued. Appropriate fluid and electrolyte management, protein supplementation, antibiotic treatment of C. difficile, and surgical evaluation should be instituted as clinically indicated.

PRECAUTIONS SECTION

General

As with other broad-spectrum antibiotics, prolonged administration of cefuroxime axetil may result in overgrowth of nonsusceptible microorganisms. If superinfection occurs during therapy, appropriate measures should be taken.

Cephalosporins, including cefuroxime axetil, should be given with caution to patients receiving concurrent treatment with potent diuretics because these diuretics are suspected of adversely affecting renal function.

Cefuroxime axetil, as with other broad-spectrum antibiotics, should be prescribed with caution in individuals with a history of colitis. The safety and effectiveness of cefuroxime axetil have not been established in patients with gastrointestinal malabsorption. Patients with gastrointestinal malabsorption were excluded from participating in clinical trials of cefuroxime axetil.

Cephalosporins may be associated with a fall in prothrombin activity. Those at risk include patients with renal or hepatic impairment or poor nutritional state, as well as patients receiving a protracted course of antimicrobial therapy, and patients previously stabilized on anticoagulant therapy. Prothrombin time should be monitored in patients at risk and exogenous Vitamin K administered as indicated.

Prescribing cefuroxime axetil in the absence of a proven or strongly suspected bacterial infection or a prophylactic indication is unlikely to provide benefit to the patient and increases the risk of the development of drug-resistant bacteria.

Diarrhea is a common problem caused by antibiotics which usually ends when the antibiotic is discontinued. Sometimes after starting treatment with antibiotics, patients can develop watery and bloody stools (with or without stomach cramps and fever) even as late as 2 or more months after having taken the last dose of the antibiotic. If this occurs, patients should contact their physician as soon as possible.

Information for Patients/Caregivers (Pediatric)

1. During clinical trials, the tablet was tolerated by pediatric patients old enough to swallow the cefuroxime axetil tablet whole. The crushed tablet has a strong, persistent, bitter taste and should not be administered to pediatric patients in this manner. Pediatric patients who cannot swallow the tablet whole should receive the oral suspension.
2. Patients should be counseled that antibacterial drugs, including cefuroxime axetil, should only be used to treat bacterial infections. They do not treat viral infections (e.g., the common cold). When cefuroxime axetil is prescribed to treat a bacterial infection, patients should be told that although it is common to feel better early in the course of therapy, the medication should be taken exactly as directed. Skipping doses or not completing the full course of therapy may: (1) decrease the effectiveness of the immediate treatment, and (2) increase the likelihood that bacteria will develop resistance and will not be treatable by cefuroxime axetil or other antibacterial drugs in the future.

Drug/Laboratory Test Interactions

A false-positive reaction for glucose in the urine may occur with copper reduction tests (Benedict’s or Fehling’s solution or with CLINITEST® tablets), but not with enzyme-based tests for glycosuria (e.g., CLINISTIX®). As a false-negative result may occur in the ferricyanide test, it is recommended that either the glucose oxidase or hexokinase method be used to determine blood/plasma glucose levels in patients receiving cefuroxime axetil. The presence of cefuroxime does not interfere with the assay of serum and urine creatinine by the alkaline picrate method.

Drug/Drug Interactions

Concomitant administration of probenecid with cefuroxime axetil tablets increases the area under the serum concentration versus time curve by 50%. The peak serum cefuroxime concentration after a 1.5 g single dose is greater when taken with 1 g of probenecid (mean = 14.8 mcg/mL) than without probenecid (mean = 12.2 mcg/mL).

Drugs that reduce gastric acidity may result in a lower bioavailability of cefuroxime axetil compared with that of fasting state and tend to cancel the effect of postprandial absorption.

In common with other antibiotics, cefuroxime axetil may affect the gut flora, leading to lower estrogen reabsorption and reduced efficacy of combined oral estrogen/progesterone contraceptives.

Carcinogenesis, Mutagenesis, Impairment of Fertility

Although lifetime studies in animals have not been performed to evaluate carcinogenic potential, no mutagenic activity was found for cefuroxime axetil in a battery of bacterial mutation tests. Positive results were obtained in an in vitro chromosome aberration assay; however, negative results were found in an in vivo micronucleus test at doses up to 1.5 g/kg. Reproduction studies in rats at doses up to 1,000 mg/kg/day (9 times the recommended maximum human dose based on mg/m2) have revealed no impairment of fertility.

PregnancyTeratogenic Effects

Pregnancy Category B. Reproduction studies have been performed in mice at doses up to 3,200 mg/kg/day (14 times the recommended maximum human dose based on mg/m2) and in rats at doses up to 1,000 mg/kg/day (9 times the recommended maximum human dose based on mg/m2) and have revealed no evidence of impaired fertility or harm to the fetus due to cefuroxime axetil. There are, however, no adequate and well-controlled studies in pregnant women. Because animal reproduction studies are not always predictive of human response, this drug should be used during pregnancy only if clearly needed.

Labor and Delivery

Cefuroxime axetil has not been studied for use during labor and delivery.

Nursing Mothers

Because cefuroxime is excreted in human milk, consideration should be given to discontinuing nursing temporarily during treatment with cefuroxime axetil.

Pediatric Use

The safety and effectiveness of cefuroxime axetil have been established for pediatric patients aged 3 months to 12 years for acute bacterial maxillary sinusitis based upon its approval in adults. Use of cefuroxime axetil in pediatric patients is supported by pharmacokinetic and safety data in adults and pediatric patients, and by clinical and microbiological data from adequate and well-controlled studies of the treatment of acute bacterial maxillary sinusitis in adults and of acute otitis media with effusion in pediatric patients. It is also supported by postmarketing adverse events surveillance (see CLINICAL PHARMACOLOGY, INDICATIONS AND USAGE, ADVERSE REACTIONS, DOSAGE AND ADMINISTRATION, and CLINICAL STUDIES).

Geriatric Use

Of the total number of subjects who received cefuroxime axetil in 20 clinical studies of cefuroxime axetil, 375 were 65 and over while 151 were 75 and over. No overall differences in safety or effectiveness were observed between these subjects and younger adult subjects. The geriatric patients reported somewhat fewer gastrointestinal events and less frequent vaginal candidiasis compared with patients aged 12 to 64 years old; however, no clinically significant differences were reported between the elderly and younger adult patients. Other reported clinical experience has not identified differences in responses between the elderly and younger adult patients.

ADVERSE REACTIONS SECTION

CEFUROXIME AXETIL TABLETS IN CLINICAL TRIALSMultiple-Dose Dosing Regimens7 to 10 Days Dosing

Using multiple doses of cefuroxime axetil tablets, 912 patients were treated with cefuroxime axetil (125 to 500 mg twice daily). There were no deaths or permanent disabilities thought related to drug toxicity. Twenty (2.2%) patients discontinued medication due to adverse events thought by the investigators to be possibly, probably, or almost certainly related to drug toxicity. Seventeen (85%) of the 20 patients who discontinued therapy did so because of gastrointestinal disturbances, including diarrhea, nausea, vomiting, and abdominal pain. The percentage of cefuroxime axetil tablet-treated patients who discontinued study drug because of adverse events was very similar at daily doses of 1,000, 500, and 250 mg (2.3%, 2.1%, and 2.2%, respectively). However, the incidence of gastrointestinal adverse events increased with the higher recommended doses.

The following adverse events were thought by the investigators to be possibly, probably, or almost certainly related to cefuroxime axetil tablets in multiple-dose clinical trials (n = 912 cefuroxime axetil-treated patients).

Table 2. Adverse Reactions— Cefuroxime Axetil Tablets Multiple-Dose Dosing Regimens—Clinical Trials
Incidence ≥1% | Diarrhea/loose stools 3.7% Nausea/vomiting 3% Transient elevation in AST 2% Transient elevation in ALT 1.6% Eosinophilia 1.1% Transient elevation in LDH 1%
Incidence <1% but >0.1% | Abdominal pain Abdominal cramps Flatulence Indigestion Headache Vaginitis Vulvar itch Rash Hives Itch Dysuria Chills Chest pain Shortness of breath Mouth ulcers Swollen tongue Sleepiness Thirst Anorexia Positive Coombs test

5-Day Experience (see CLINICAL STUDIES section)

In clinical trials using cefuroxime axetil in a dose of 250 mg twice daily in the treatment of secondary bacterial infections of acute bronchitis, 399 patients were treated for 5 days and 402 patients were treated for 10 days. No difference in the occurrence of adverse events was found between the 2 regimens.

In Clinical Trials for Early Lyme Disease With 20 Days Dosing

Two multicenter trials assessed cefuroxime axetil tablets 500 mg twice a day for 20 days. The most common drug-related adverse experiences were diarrhea (10.6% of patients), Jarisch-Herxheimer reaction (5.6%), and vaginitis (5.4%). Other adverse experiences occurred with frequencies comparable to those reported with 7 to 10 days dosing.

Single-Dose Regimen for Uncomplicated Gonorrhea

In clinical trials using a single dose of cefuroxime axetil tablets, 1,061 patients were treated with the recommended dosage of cefuroxime axetil (1,000 mg) for the treatment of uncomplicated gonorrhea. There were no deaths or permanent disabilities thought related to drug toxicity in these studies.

The following adverse events were thought by the investigators to be possibly, probably, or almost certainly related to cefuroxime axetil in 1,000 mg single-dose clinical trials of cefuroxime axetil tablets in the treatment of uncomplicated gonorrhea conducted in the United States.

Table 3. Adverse Reactions— Cefuroxime Axetil Tablets 1-g Single-Dose Regimen for Uncomplicated Gonorrhea—Clinical Trials
Incidence ≥1% | Nausea/vomiting 6.8% Diarrhea 4.2%
Incidence <1% but >0.1% | Abdominal pain Dyspepsia Erythema Rash Pruritus Vaginal candidiasis Vaginal itch Vaginal discharge Headache Dizziness Somnolence Muscle cramps Muscle stiffness Muscle spasm of neck Tightness/pain in chest Bleeding/pain in urethra Kidney pain Tachycardia Lockjaw-type reaction

POSTMARKETING EXPERIENCE WITH CEFUROXIME AXETIL PRODUCTS

In addition to adverse events reported during clinical trials, the following events have been identified during clinical practice in patients treated with cefuroxime axetil tablets or with cefuroxime axetil for oral suspension and were reported spontaneously. Data are generally insufficient to allow an estimate of incidence or to establish causation.

General: The following hypersensitivity reactions have been reported: anaphylaxis, angioedema, pruritus, rash, serum sickness-like reaction, urticaria.

Gastrointestinal: Pseudomembranous colitis (see WARNINGS).

Hematologic: Hemolytic anemia, leukopenia, pancytopenia, thrombocytopenia, and increased prothrombin time.

Hepatic: Hepatic impairment including hepatitis and cholestasis, jaundice.

Neurologic: Seizure.

Skin: Erythema multiforme, Stevens-Johnson syndrome, toxic epidermal necrolysis.

Urologic: Renal dysfunction.

CEPHALOSPORIN-CLASS ADVERSE REACTIONS

In addition to the adverse reactions listed above that have been observed in patients treated with cefuroxime axetil, the following adverse reactions and altered laboratory tests have been reported for cephalosporin-class antibiotics: toxic nephropathy, aplastic anemia, hemorrhage, increased BUN, increased creatinine, false-positive test for urinary glucose, increased alkaline phosphatase, neutropenia, elevated bilirubin, and agranulocytosis.

Several cephalosporins have been implicated in triggering seizures, particularly in patients with renal impairment when the dosage was not reduced (see DOSAGE AND ADMINISTRATION and OVERDOSAGE). If seizures associated with drug therapy occur, the drug should be discontinued. Anticonvulsant therapy can be given if clinically indicated.

OVERDOSAGE SECTION

Overdosage of cephalosporins can cause cerebral irritation leading to convulsions. Serum levels of cefuroxime can be reduced by hemodialysis and peritoneal dialysis.

DOSAGE AND ADMINISTRATION

NOTE: CEFUROXIME AXETIL TABLETS AND CEFUROXIME AXETIL FOR ORAL SUSPENSION ARE NOT BIOEQUIVALENT AND ARE NOT SUBSTITUTABLE ON A MILLIGRAM-PER-MILLIGRAM BASIS (SEE CLINICAL PHARMACOLOGY).

Table 4. Cefuroxime Axetil Tablets (May be administered without regard to meals.)
Population/Infection | Dosage | Duration (days)
Adolescents and Adults (13 years and older)
Pharyngitis/tonsillitis | 250 mg b.i.d. | 10
Acute bacterial maxillary sinusitis | 250 mg b.i.d. | 10
Acute bacterial exacerbations of chronic bronchitis | 250 or 500 mg b.i.d. | 10*
Secondary bacterial infections of acute bronchitis | 250 or 500 mg b.i.d. | 5-10
Uncomplicated skin and skin-structure infections | 250 or 500 mg b.i.d. | 10
Uncomplicated urinary tract infections | 250 mg b.i.d. | 7-10
Uncomplicated gonorrhea | 1,000 mg once | single dose
Early Lyme disease | 500 mg b.i.d. | 20
Pediatric Patients (who can swallow tablets whole)
Acute otitis media | 250 mg b.i.d. | 10
Acute bacterial maxillary sinusitis | 250 mg b.i.d. | 10
*The safety and effectiveness of cefuroxime axetil administered for less than 10 days in patients with acute exacerbations of chronic bronchitis have not been established.

Patients With Renal Failure

The safety and efficacy of cefuroxime axetil in patients with renal failure have not been established. Since cefuroxime is renally eliminated, its half-life will be prolonged in patients with renal failure.

HOW SUPPLIED SECTION

Cefuroxime Axetil Tablets USP, 125 mg of cefuroxime (as cefuroxime axetil), are white to off-white, uncoated, capsule shaped tablets with “A32” debossed on one side and plain on the other side.

20 Tablets/Bottle NDC 65862-033-20

60 Tablets/Bottle NDC 65862-033-60

Cefuroxime Axetil Tablets, USP 250 mg of cefuroxime (as cefuroxime axetil), are white to off-white, uncoated, capsule-shaped tablets with “A33” debossed on one side and plain on the other side.

20 Tablets/Bottle NDC 65862-034-20

60 Tablets/Bottle NDC 65862-034-60

Cefuroxime Axetil Tablets, USP 500 mg of cefuroxime (as cefuroxime axetil), are white to off-white, uncoated, capsule-shaped tablets with “A34” debossed on one side and plain on the other side.

20 Tablets/Bottle NDC 65862-035-20

60 Tablets/Bottle NDC 65862-035-60

Store at 20° to 25°C (68° to 77°F); excursions permitted to 15° to 30°C (59° to 86°F) [see USP Controlled Room Temperature]. Replace cap securely after each opening.

CLINICAL STUDIES SECTION

Cefuroxime Axetil TabletsAcute Bacterial Maxillary Sinusitis

One adequate and well-controlled study was performed in patients with acute bacterial maxillary sinusitis. In this study each patient had a maxillary sinus aspirate collected by sinus puncture before treatment was initiated for presumptive acute bacterial sinusitis. All patients had to have radiographic and clinical evidence of acute maxillary sinusitis. As shown in the following summary of the study, the general clinical effectiveness of cefuroxime axetil tablets was comparable to an oral antimicrobial agent that contained a specific betalactamase inhibitor in treating acute maxillary sinusitis. However, sufficient microbiology data were obtained to demonstrate the effectiveness of cefuroxime axetil tablets in treating acute bacterial maxillary sinusitis due only to Streptococcus pneumoniae or non-beta-lactamase–producing Haemophilus influenzae. An insufficient number of beta-lactamase–producing Haemophilus influenzae and Moraxella catarrhalis isolates were obtained in this trial to adequately evaluate the effectiveness of cefuroxime axetil tablets in the treatment of acute bacterial maxillary sinusitis due to these 2 organisms.

This study enrolled 317 adult patients, 132 patients in the United States and 185 patients in South America. Patients were randomized in a 1:1 ratio to cefuroxime axetil 250 mg twice daily or an oral antimicrobial agent that contained a specific beta-lactamase inhibitor. An intent-to-treat analysis of the submitted clinical data yielded the following results:

Table 5. Clinical Effectiveness of Cefuroxime Axetil Tablets Compared to Beta-Lactamase Inhibitor-Containing Control Drug in the Treatment of Acute Bacterial Maxillary Sinusitis
 | U.S. Patients* | South American Patients†
Cefuroxime Axetil (n = 49) | Control (n = 43) | Cefuroxime Axetil (n = 87) | Control (n = 89)
Clinical success (cure + improvement) | 65% | 53% | 77% | 74%
Clinical cure | 53% | 44% | 72% | 64%
Clinical improvement | 12% | 9% | 5% | 10%
*95% Confidence interval around the success difference [-0.08, +0.32].
†95% Confidence interval around the success difference [-0.1, +0.16].

In this trial and in a supporting maxillary puncture trial, 15 evaluable patients had non-beta-lactamase–producing Haemophilus influenzae as the identified pathogen. Ten (10) of these 15 patients (67%) had their pathogen (non-beta-lactamase-producing Haemophilus influenzae) eradicated. Eighteen (18) evaluable patients had Streptococcus pneumoniae as the identified pathogen. Fifteen (15) of these 18 patients (83%) had their pathogen (Streptococcus pneumoniae) eradicated.

Safety

The incidence of drug-related gastrointestinal adverse events was statistically significantly higher in the control arm (an oral antimicrobial agent that contained a specific beta-lactamase inhibitor) versus the cefuroxime axetil arm (12% versus 1%, respectively; P<.001), particularly drug-related diarrhea (8% versus 1%, respectively; P = .001).

Early Lyme Disease

Two adequate and well-controlled studies were performed in patients with early Lyme disease. In these studies all patients had to present with physician-documented erythema migrans, with or without systemic manifestations of infection. Patients were randomized in a 1:1 ratio to a 20-day course of treatment with cefuroxime axetil 500 mg twice daily or doxycycline 100 mg 3 times daily. Patients were assessed at 1 month posttreatment for success in treating early Lyme disease (Part I) and at 1 year posttreatment for success in preventing the progression to the sequelae of late Lyme disease (Part II).

A total of 355 adult patients (181 treated with cefuroxime axetil and 174 treated with doxycycline) were enrolled in the 2 studies. In order to objectively validate the clinical diagnosis of early Lyme disease in these patients, 2 approaches were used:1) blinded expert reading of photographs, when available, of the pretreatment erythema migrans skin lesion; and 2) serologic confirmation (using enzyme-linked immunosorbent assay [ELISA] and immunoblot assay [“Western” blot]) of the presence of antibodies specific to Borrelia burgdorferi, the etiologic agent of Lyme disease. By these procedures, it was possible to confirm the physician diagnosis of early Lyme disease in 281 (79%) of the 355 study patients. The efficacy data summarized below are specific to this “validated” patient subset, while the safety data summarized below reflect the entire patient population for the 2 studies.

Analysis of the submitted clinical data for evaluable patients in the “validated” patient subset yielded the following results:

Table 6. Clinical Effectiveness of Cefuroxime Axetil Tablets Compared to Doxycycline in the Treatment of Early Lyme Disease
 | Part I (1 Month Posttreatment)* | Part II (1 Year Posttreatment)†
Cefuroxime Axetil (n = 125) | Doxycycline (n = 108) | Cefuroxime Axetil (n = 105‡) | Doxycycline (n = 83‡)
Satisfactory clinical outcome§ | 91% | 93% | 84% | 87%
Clinical cure/success | 72% | 73% | 73% | 73%
Clinical improvement | 19% | 19% | 10% | 13%
* 95% confidence interval around the satisfactory difference for Part I (-0.08, +0.05).
† 95% confidence interval around the satisfactory difference for Part II (-0.13, +0.07).
‡ n’s include patients assessed as unsatisfactory clinical outcomes (failure + recurrence) in Part I (cefuroxime axetil tablets - 11 [5 failure, 6 recurrence]; doxycycline - 8 [6 failure, 2 recurrence]).
§ Satisfactory clinical outcome includes cure + improvement (Part I) and success + improvement (Part II).

Cefuroxime axetil and doxycycline were effective in prevention of the development of sequelae of late Lyme disease.

Safety

Drug-related adverse events affecting the skin were reported significantly more frequently by patients treated with doxycycline than by patients treated with cefuroxime axetil (12% versus 3%, respectively; P = .002), primarily reflecting the statistically significantly higher incidence of drug-related photosensitivity reactions in the doxycycline arm versus the cefuroxime axetil arm (9% versus 0%, respectively; P<.001). While the incidence of drug-related gastrointestinal adverse events was similar in the 2 treatment groups (cefuroxime axetil - 13%; doxycycline - 11%), the incidence of drug-related diarrhea was statistically significantly higher in the cefuroxime axetil arm versus the doxycycline arm (11% versus 3%, respectively; P = .005).

Secondary Bacterial Infections of Acute Bronchitis

Four randomized, controlled clinical studies were performed comparing 5 days versus 10 days of cefuroxime axetil for the treatment of patients with secondary bacterial infections of acute bronchitis. These studies enrolled a total of 1,253 patients (CAE-516 n = 360; CAE-517 n = 177; CAEA4001 n = 362; CAEA4002 n = 354). The protocols for CAE-516 and CAE-517 were identical and compared cefuroxime axetil 250 mg twice daily for 5 days, cefuroxime axetil 250 mg twice daily for 10 days, and AUGMENTIN® 500 mg 3 times daily for 10 days. These 2 studies were conducted simultaneously. CAEA4001 and CAEA4002 compared cefuroxime axetil 250 mg twice daily for 5 days, cefuroxime axetil 250 mg twice daily for 10 days, and CECLOR® 250 mg 3 times daily for 10 days. They were otherwise identical to CAE-516 and CAE-517 and were conducted over the following 2 years. Patients were required to have polymorphonuclear cells present on the Gram stain of their screening sputum specimen, but isolation of a bacterial pathogen from the sputum culture was not required for inclusion. The following table demonstrates the results of the clinical outcome analysis of the pooled studies CAE-516/CAE-517 and CAEA4001/CAEA4002, respectively:

Table 7. Clinical Effectiveness of Cefuroxime Axetil Tablets 250 mg Twice Daily in Secondary Bacterial Infections of Acute Bronchitis: Comparison of 5 Versus 10 Days’ Treatment Duration
 | CAE-516 and CAE-517* | CAEA4001 and CAEA4002†
5 day (n = 127) | 10 day (n = 139) | 5 day (n = 173) | 10 day (n = 192)
Clinical success (cure + improvement) | 80% | 87% | 84% | 82%
Clinical cure | 61% | 70% | 73% | 72%
Clinical improvement | 19% | 17% | 11% | 10%
*95% Confidence interval around the success difference [-0.164, +0.029].
† 95% Confidence interval around the success difference [-0.061, +0.103].

The response rates for patients who were both clinically and bacteriologically evaluable were consistent with those reported for the clinically evaluable patients.

Safety

In these clinical trials, 399 patients were treated with cefuroxime axetil for 5 days and 402 patients with cefuroxime axetil for 10 days. No difference in the occurrence of adverse events was observed between the 2 regimens.

REFERENCES SECTION

1. National Committee for Clinical Laboratory Standards. Methods for Dilution Antimicrobial Susceptibility Tests for Bacteria that Grow Aerobically. 3rd ed. Approved Standard NCCLS Document M7-A3, Vol. 13, No. 25. Villanova, Pa: NCCLS; 1993.
2. National Committee for Clinical Laboratory Standards. Performance Standards for Antimicrobial Disk Susceptibility Tests. 4th ed. Approved Standard NCCLS Document M2-A4, Vol. 10, No. 7. Villanova, Pa: NCCLS; 1990.

AUGMENTIN® and CECLOR® are registered trademarks of GlaxoSmithKline.

CLINITEST and CLINISTIX are registered trademarks of Ames Division, Miles Laboratories, Inc.

Manufactured for:

Aurobindo Pharma USA, Inc.

2400 Route 130 North

Dayton, NJ 08810

Manufactured by:

Aurobindo Pharma Limited

Chitkul (v)-502 307, A.P., India

Rev. 09/07

PACKAGE LABEL-PRINCIPAL DISPLAY PANEL - 125 mg (60 Tablet Bottle)

NDC 65862-033-60

Cefuroxime Axetil

Tablets USP

125 mg*

Rx only 60 Tablets

AUROBINDO